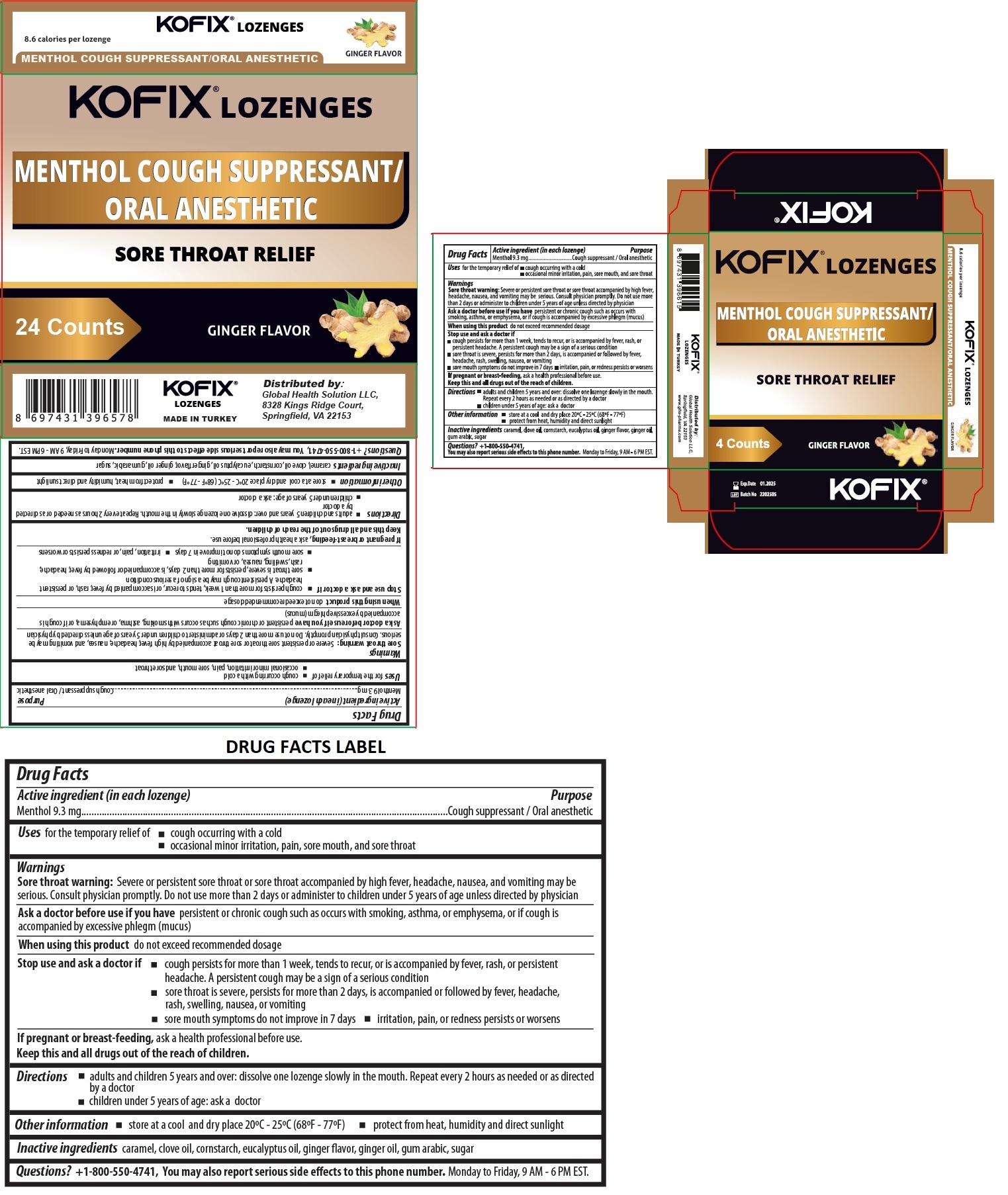 DRUG LABEL: KOFIX GINGER
NDC: 82340-001 | Form: LOZENGE
Manufacturer: Global Health Solution LLC
Category: otc | Type: HUMAN OTC DRUG LABEL
Date: 20220107

ACTIVE INGREDIENTS: MENTHOL, UNSPECIFIED FORM 9.3 mg/1 1
INACTIVE INGREDIENTS: CARAMEL; CLOVE OIL; STARCH, CORN; EUCALYPTUS OIL; GINGER OIL; ACACIA; SUCROSE

KOFIX® LOZENGES

Active ingredient (in each lozenge)

Menthol 9.3 mg

Purpose

Cough suppressant / Oral anesthetic

Uses

for the temporary relief of
• cough occurring with a cold
• occasional minor irritation, pain, sore mouth, and sore throat

Warnings

Sore throat warning: Severe or persistent sore throat or sore throat accompanied by high fever, headache, nausea, and vomiting may be serious. Consult physician promptly. Do not use more than 2 days or administer to children under 5 years of age unless directed by physician

Ask a doctor before use if you have persistent or chronic cough such as occurs with smoking, asthma, or emphysema, or if cough is accompanied by excessive phlegm (mucus)

When using this product do not exceed recommended dosage

Stop use and ask a doctor if
• cough persists for more than 1 week, tends to recur, or is accompanied by fever, rash, or persistent headache. A persistent cough may be a sign of a serious condition
• sore throat is severe, persists for more than 2 days, is accompanied or followed by fever, headache, rash, swelling, nausea, or vomiting
• sore mouth symptoms do not improve in 7 days • irritation, pain, or redness persists or worsens

If pregnant or breast-feeding, ask a health professional before use.

KEEP OUT OF REACH OF CHILDREN

Keep this and all drugs out of the reach of children.

Directions

• adults and children 5 years and over: dissolve one lozenge slowly in the mouth. Repeat every 2 hours as needed or as directed by a doctor
• children under 5 years of age: ask a doctor

Other information

• store at a cool and dry place 20ºC - 25ºC (68ºF - 77ºF) • protect from heat, humidity and direct sunlight

Inactive ingredients

caramel, clove oil, cornstarch, eucalyptus oil, ginger flavor, ginger oil, gum arabic, sugar

Questions?

+1-800-550-4741, You may also report serious side effects to this phone number. Monday to Friday, 9 AM - 6 PM EST.

MENTHOL COUGH SUPPRESSANT/ORAL ANESTHETIC

SORE THROAT RELIEF

GINGER FLAVOR

8.6 calories per lozenge

MADE IN TURKEY

Distributed by:
Global Health Solution LLC,
8328 Kings Ridge Court,
Springfield, VA 22153